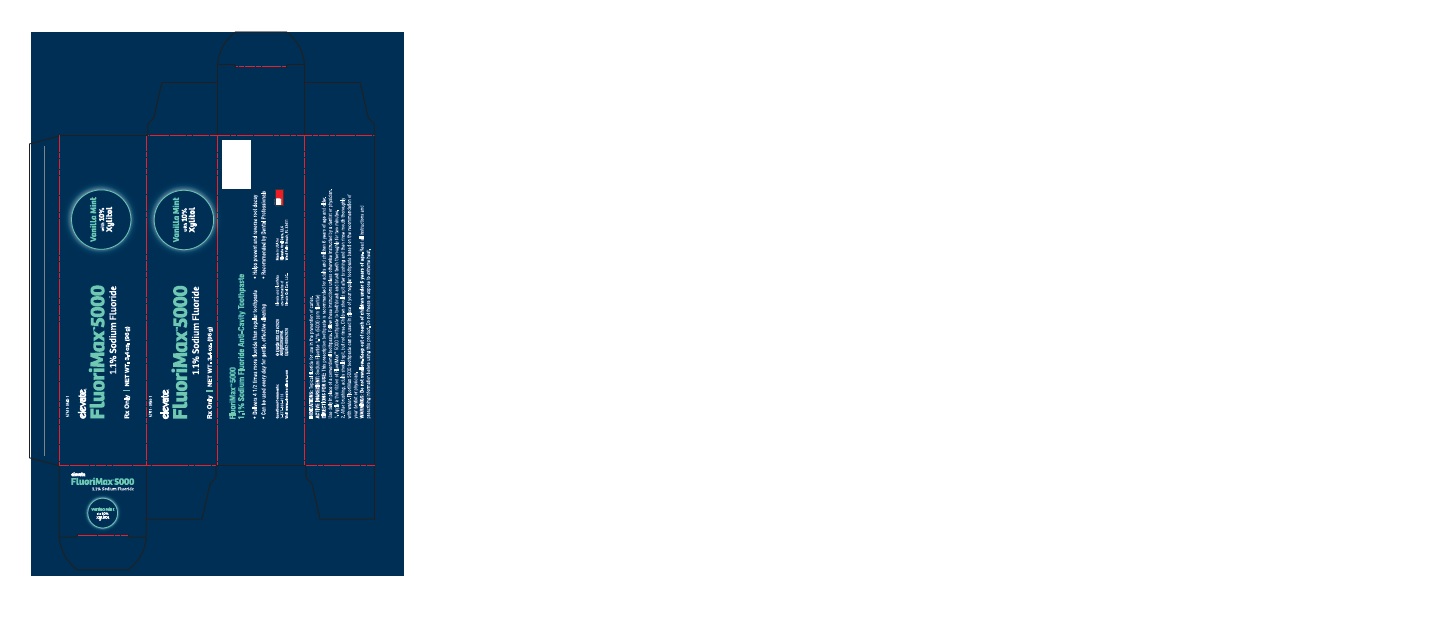 DRUG LABEL: FluoriMax 5000
NDC: 57511-0504 | Form: PASTE, DENTIFRICE
Manufacturer: Elevate Oral Care
Category: prescription | Type: HUMAN PRESCRIPTION DRUG LABEL
Date: 20200901

ACTIVE INGREDIENTS: SODIUM FLUORIDE 1.1 g/100 g

FluoriMax 5000 1.1% Sodium Fluoride Toothpaste

Warnings

Do not swallow. Keep out of reach of children under 6 years of age. Read instructions and prescribing information before using product.